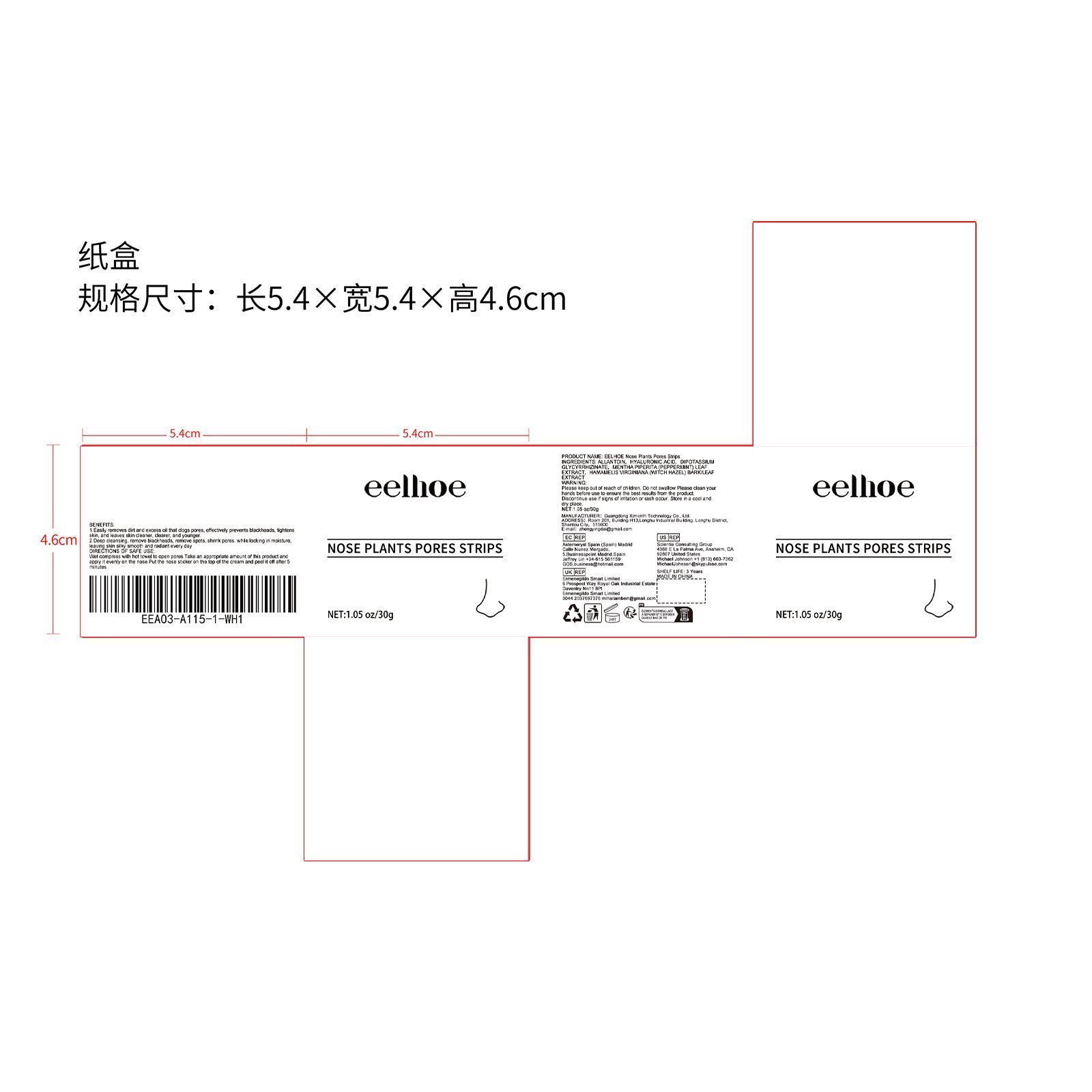 DRUG LABEL: Nose Plants Pores Strips
NDC: 84660-014 | Form: STRIP
Manufacturer: Guangdong Ximonth Technology Co., Ltd.
Category: otc | Type: HUMAN OTC DRUG LABEL
Date: 20240909

ACTIVE INGREDIENTS: HAMAMELIS VIRGINIANA TOP 3 g/30 g; HYALURONIC ACID 7.5 g/30 g; MENTHA PIPERITA LEAF 4.5 g/30 g
INACTIVE INGREDIENTS: GLYCYRRHIZINATE DIPOTASSIUM 6 g/30 g; ALLANTOIN 9 g/30 g

Active Ingredient(s)

HYALURONIC ACID、DIPOTASSIUM GLYCYRRHIZINATE、MENTHA PIPERITA (PEPPERMINT) LEAF EXTRACT、HAMAMELIS VIRGINIANA (WITCH HAZEL) BARK/LEAF EXTRACT

Purpose

1.Easily removes dirt and excess oil that clogs pores, effectively prevents blackheads, tightens skin, and leaves skin cleaner, clearer, and younger.2.Deep cleansing, remove blackheads, remove spots, shrink pores. while locking in moisture, leaving skin silky smooth and radiant every day

Use

Wet compress with hot towel to open pores.Take an appropriate amount of this product and apply it evenly on the nose Put the nose sticker on the top of the cream and peel it off after 5 minutes.

Warnings

Please keep out of reach of children.Do not swallow.Please clean your hands before use to ensure the best results from the product.Discontinue use if signs of irritation or rash occur.Store in a cool and dry place.

Do not use

Discontinue use if signs of irritation or rash occur.

STOP USE

Discontinue use if signs of irritation or rash occur.

KEEP OUT OF REACH OF CHILDREN

Please keep out of reach of children. Do not swallow.

STORAGE AND HANDLING

Avoid freezing and excessive heat above 40C (104F) ）

Store in a cool and dry place.

INACTIVE INGREDIENT

ALLANTOIN